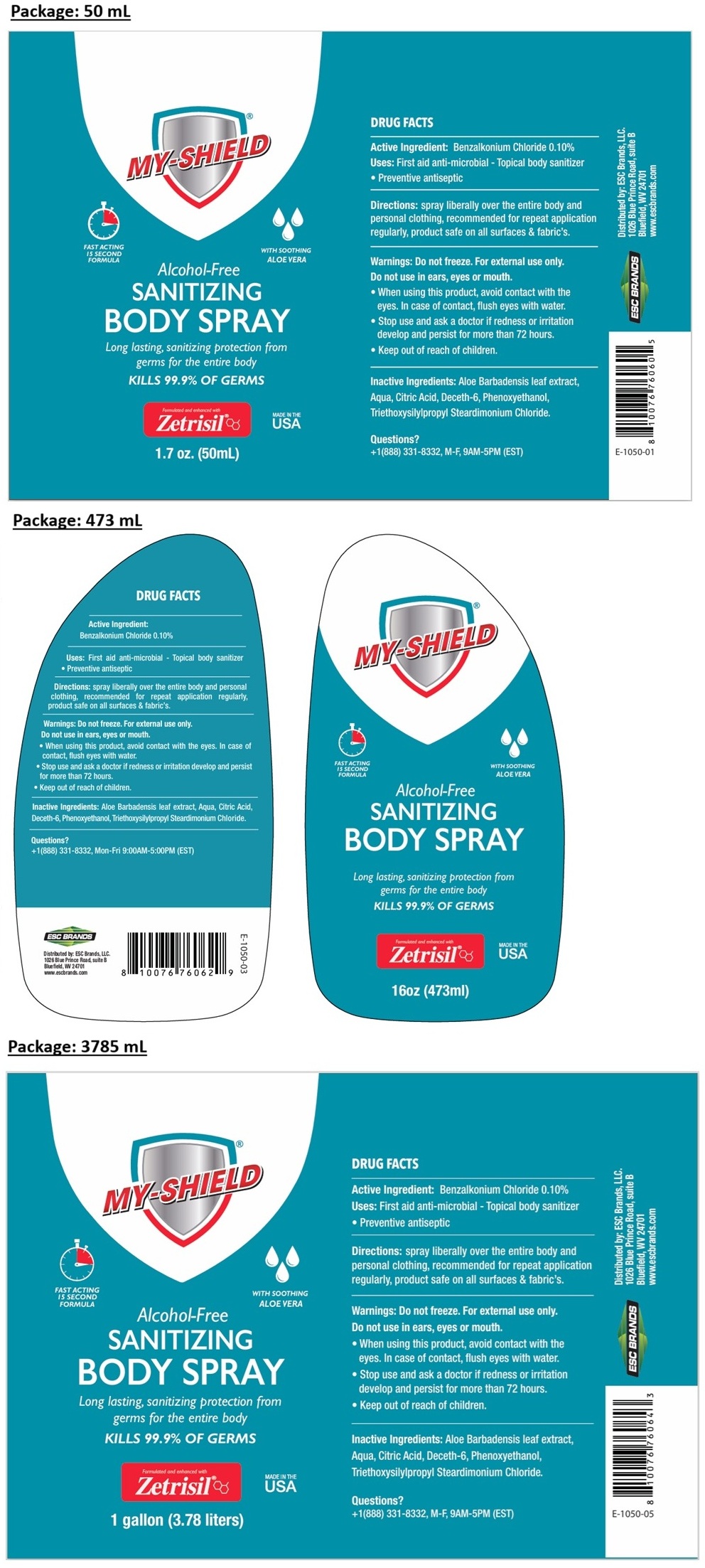 DRUG LABEL: My-Shield Sanitizing Body
NDC: 71884-009 | Form: SPRAY
Manufacturer: Enviro Specialty Chemicals Inc
Category: otc | Type: HUMAN OTC DRUG LABEL
Date: 20260129

ACTIVE INGREDIENTS: BENZALKONIUM CHLORIDE 0.1 g/100 mL
INACTIVE INGREDIENTS: ALOE VERA LEAF; WATER; CITRIC ACID MONOHYDRATE; DECETH-6; PHENOXYETHANOL; TRIETHOXYSILYLPROPYL STEARDIMONIUM CHLORIDE

MY-SHIELD SANITIZING BODY SPRAY

Active Ingredient:

Benzalkonium Chloride 0.10%

Purpose:

Antiseptic

Uses:

First aid anti-microbial - Topical body sanitizer • Preventive antiseptic

Directions:

Spray liberally over the entire body and personal clothing, recommended for repeat application regularly, product safe on all surfaces & fabric’s.

Warnings:

Do not freeze. For external use only.

Do not use in ears, eyes or mouth.

• When using this product, avoid contact with the eyes. In case of contact, flush eyes with water.

• Stop use and ask a doctor if redness or irritation develop and persist for more than 72 hours.

• Keep out of reach of children.

Inactive Ingredients:

Aloe Barbadensis leaf extract, Aqua, Citric Acid, Deceth-6, Phenoxyethanol, Triethoxysilylpropyl Steardimonium Chloride.

Questions?

+1(888) 331-8332, M-F, 9AM-5PM (EST)

FAST ACTING 15 SECOND FORMULA

WITH SOOTHING ALOE VERA

Alcohol-Free

Long lasting, sanitizing protection from germs for the entire body

KILLS 99.99% OF GERMS

Formulated and enhanced with Zetrisil®

MADE IN THE USA

Distributed by: ESC Brands, LLC.
1026 Blue Prince Road, suite B
Bluefield, WV 24701
www.escbrands.com